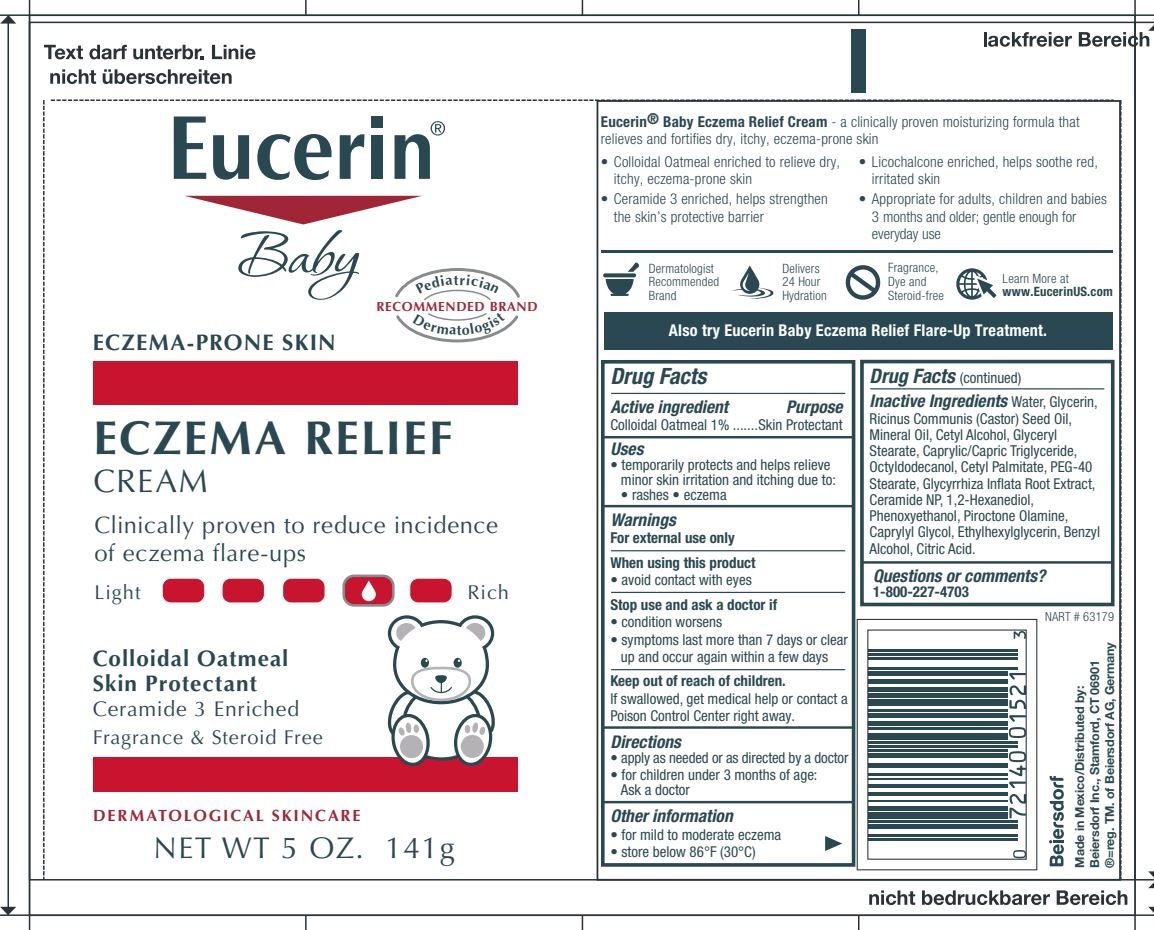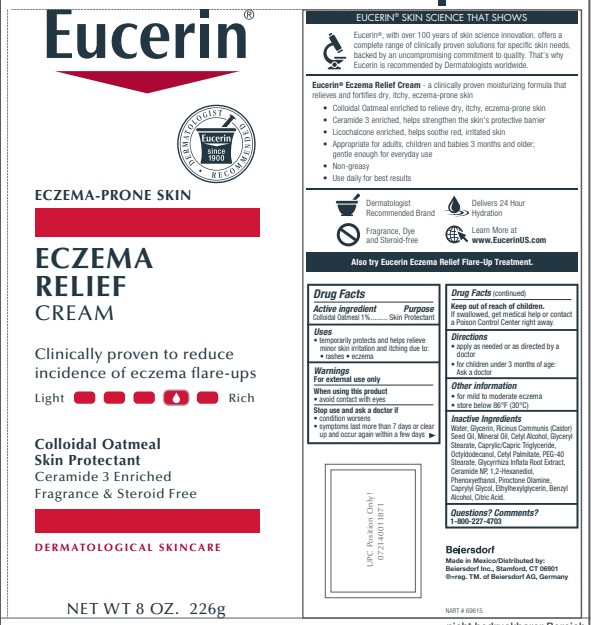 DRUG LABEL: Eucerin Eczema Relief Body
NDC: 10356-365 | Form: CREAM
Manufacturer: Beiersdorf Inc
Category: otc | Type: HUMAN OTC DRUG LABEL
Date: 20251231

ACTIVE INGREDIENTS: OATMEAL 1 g/100 g
INACTIVE INGREDIENTS: CAPRYLYL GLYCOL; ETHYLHEXYLGLYCERIN; BENZYL ALCOHOL; CITRIC ACID MONOHYDRATE; WATER; PIROCTONE OLAMINE; GLYCERIN; CASTOR OIL; MINERAL OIL; CETYL ALCOHOL; GLYCERYL MONOSTEARATE; MEDIUM-CHAIN TRIGLYCERIDES; OCTYLDODECANOL; CETYL PALMITATE; PEG-40 STEARATE; GLYCYRRHIZA INFLATA ROOT; CERAMIDE 3; 1,2-HEXANEDIOL; PHENOXYETHANOL

Eucerin Eczema Relief Body Creme

Active ingredients
Colloidal Oatmeal 1%

Warnings
For external use only

When using this product avoid contact with eyes

Stop use and ask a doctor if
condition worsens
symptoms last more than 7 days or clear up and occur again within a few days

Keep out of reach of children. If swallowed, get medical help or
contact a Poison Control Center right away.

Uses
temporarily protects and helps relieve minor skin irritation and itching
due to rashes, eczema

Directions
Apply as needed

Questions or comments?
1-800-227-4703

Inactive Ingredients
Water, Glycerin, Ricinus Communis (Castor) Seed Oil,
Mineral Oil, Cetyl Alcohol, Glyceryl Stearate, Caprylic/Capric Triglyceride,
Octyldodecanol, Cetyl Palmitate, PEG-40 Stearate, Glycyrrhiza Inflata
Root Extract, Ceramide 3, 1,2-Hexanediol, Phenoxyethanol, Piroctone
Olamine, Caprylyl Glycol, Ethylhexylglycerin, Benzyl Alcohol, Citric Acid.

PURPOSE

Skin protectant

PACKAGE LABEL

Eucerin

Eczema Relief Body Creme

Colloidal Oatmeal Skin Protectant

Ceramide 3 enriched

Clinically proven to reduce incidence of eczema flare ups

Fragrance & Steroid Free

Dermatological Skincare

Dermatologist recommended brand

Eucerin Baby

Eczema Relief Body Creme

Clinically proven to reduce incidence of eczema flare ups

Colloidal Oatmeal Skin Protectant

Ceramide 3 Enriched

Fragrance & Steroid Free

Dermatological Skincare

Pediatrician and Dermatologist recommended brand